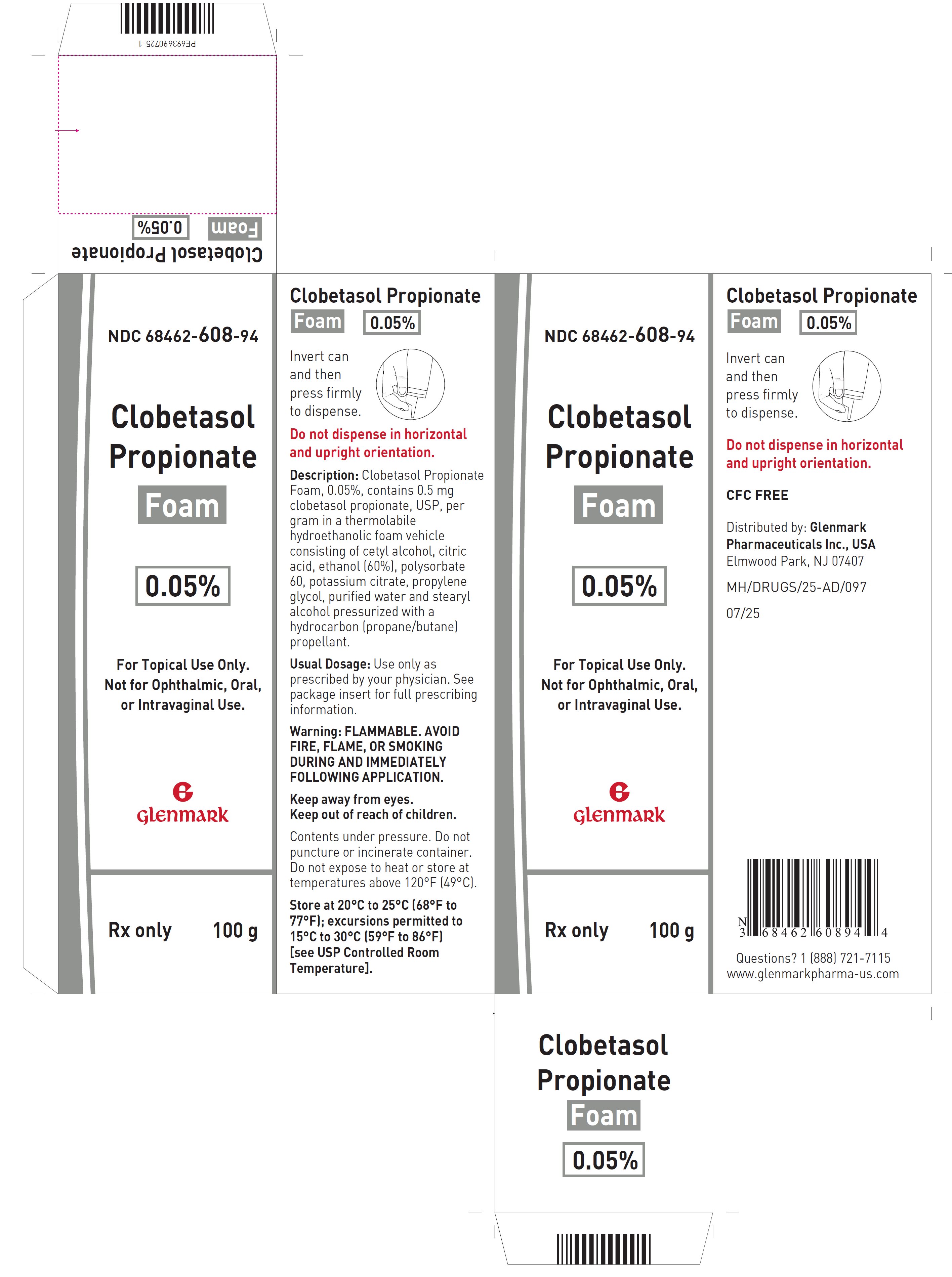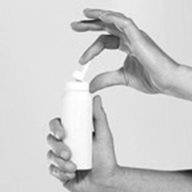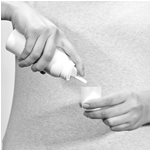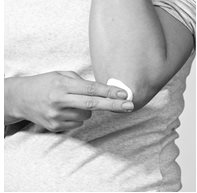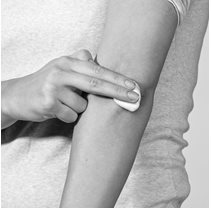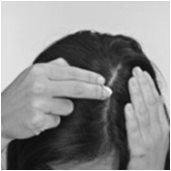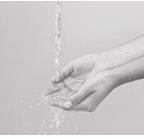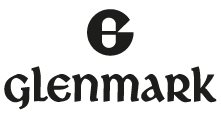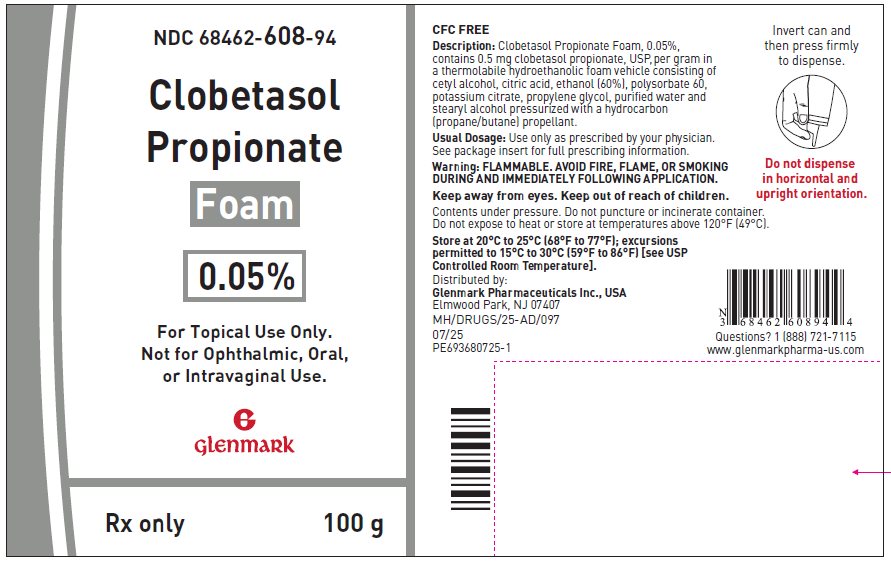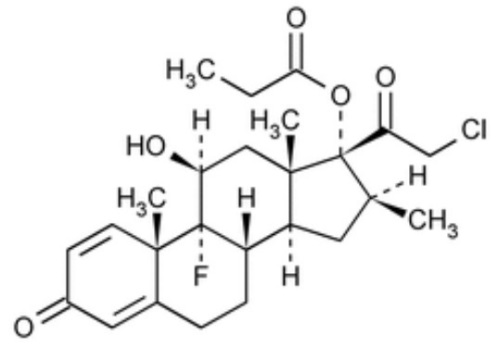 DRUG LABEL: Clobetasol Propionate
NDC: 68462-608 | Form: AEROSOL, FOAM
Manufacturer: Glenmark Pharmaceuticals Inc., USA
Category: prescription | Type: HUMAN PRESCRIPTION DRUG LABEL
Date: 20260129

ACTIVE INGREDIENTS: CLOBETASOL PROPIONATE 0.5 mg/1 g
INACTIVE INGREDIENTS: CETYL ALCOHOL; ANHYDROUS CITRIC ACID; ALCOHOL; POLYSORBATE 60; POTASSIUM CITRATE; PROPYLENE GLYCOL; WATER; STEARYL ALCOHOL

HIGHLIGHTS OF PRESCRIBING INFORMATION

These highlights do not include all the information needed to use CLOBETASOL PROPIONATE FOAM safely and effectively. See full prescribing information for CLOBETASOL PROPIONATE FOAM.
CLOBETASOL PROPIONATE foam, for topical use
Initial U.S. Approval: 1985

1 INDICATIONS AND USAGE

Clobetasol propionate foam is a corticosteroid indicated for treatment of moderate to severe plaque psoriasis of the scalp and mild to moderate plaque psoriasis of non-scalp regions of the body excluding the face and intertriginous areas in patients 12 years and older. (1)

2 DOSAGE AND ADMINISTRATION

- Apply a thin layer to the affected skin areas twice daily. (2)
- Limit treatment to 2 consecutive weeks. (2)
- Do not use more than 50 grams per week or more than 21 capfuls per week. (2)
- Discontinue therapy when control is achieved. (2)
- Do not use with occlusive dressings unless directed by physician. (2)
- Avoid use on the face, groin, or axillae, or if skin atrophy is present at the treatment site. (2)

3 DOSAGE FORMS AND STRENGTHS

- Foam, 0.05% (3)

4 CONTRAINDICATIONS

- None (4)

5 WARNINGS AND PRECAUTIONS

- Clobetasol propionate foam can cause reversible HPA axis suppression with the potential for glucocorticosteroid insufficiency during and after withdrawal of treatment. Risk factors include the use of high-potency topical corticosteroid, use over a large surface area or to areas under occlusion, prolonged use, altered skin barrier, liver failure, and use in pediatric patients. Modify use should HPA axis suppression develop. (5.1, 8.4)
- Clobetasol propionate foam may increase the risk of cataract and glaucoma. If visual symptoms occur, consider referral to an ophthalmologist. (5.2)
- Clobetasol propionate foam is flammable. Avoid fire, flame, or smoking during and immediately following application. (5.4)

6 ADVERSE REACTIONS

Most common adverse reactions (≥ 4%) are application site burning and other application site reactions. (6.1)

To report SUSPECTED ADVERSE REACTIONS, contact Glenmark Pharmaceuticals Inc., USA at 1 (888) 721-7115 or FDA at 1-800-FDA-1088 or www.fda.gov/medwatch.

FULL PRESCRIBING INFORMATION

1 INDICATIONS AND USAGE

Clobetasol propionate foam is a corticosteroid indicated for treatment of moderate to severe plaque psoriasis of the scalp and mild to moderate plaque psoriasis of non-scalp regions of the body excluding the face and intertriginous areas in patients 12 years and older.

2 DOSAGE AND ADMINISTRATION

Apply a thin layer of clobetasol propionate foam to the affected skin areas twice daily.

clobetasol propionate foam is a super-high-potency topical corticosteroid; therefore, limit treatment to 2 consecutive weeks. Patients should not use greater than 50 grams per week or more than 21 capfuls per week because of the potential for the drug to suppress the hypothalamic-pituitary-adrenal (HPA) axis [see Warnings and Precautions (5.1)].

Therapy should be discontinued when control is achieved.

Clobetasol propionate foam should not be used with occlusive dressings unless directed by a physician.

Clobetasol propionate foam is for topical use only. It is not for oral, ophthalmic, or intravaginal use.

Avoid contact with eyes. Wash hands after each application.

Avoid use on the face, groin, or axillae, or if skin atrophy is present at the treatment site.

3 DOSAGE FORMS AND STRENGTHS

Clobetasol Propionate Foam, 0.05% contains 0.5 mg of clobetasol propionate, USP per gram.

4 CONTRAINDICATIONS

None.

5 WARNINGS AND PRECAUTIONS

5.1 Effects on Endocrine System

Clobetasol propionate foam can cause reversible hypothalamic-pituitary-adrenal (HPA) axis suppression with the potential for glucocorticosteroid insufficiency. This may occur during treatment or after withdrawal of treatment. Factors that predispose a patient to HPA axis suppression include the use of high-potency steroids, large treatment surface areas, prolonged use, use of occlusive dressings, altered skin barrier, liver failure, and young age. Evaluation for HPA axis suppression may be done by using the adrenocorticotropic hormone (ACTH) stimulation test.

In a trial evaluating the effects of clobetasol propionate foam on the HPA axis, 13 subjects applied clobetasol propionate foam to at least 20% of involved body surface area for 14 days. HPA axis suppression was identified in 5 out of 13 subjects (38%) [see Clinical Pharmacology (12.2)].

If HPA axis suppression is documented, gradually withdraw the drug, reduce the frequency of application, or substitute with a less potent corticosteroid.

Cushing’s syndrome and hyperglycemia may also occur due to the systemic effects of the topical corticosteroid. These complications are rare and generally occur after prolonged exposure to excessively large doses, especially of high-potency topical corticosteroids.

Pediatric patients may be more susceptible to systemic toxicity due to their larger skin surface to body mass ratios [see Use in Specific Populations (8.4)].

5.2 Ophthalmic Adverse Reactions

Use of topical corticosteroids, including clobetasol propionate foam, may increase the risks of glaucoma and posterior subcapsular cataract. Glaucoma and cataracts have been reported in postmarketing experience with the use of topical corticosteroid products, including topical clobetasol products.

Avoid contact of clobetasol propionate foam with eyes. Advise patients to report any visual symptoms and consider referral to an ophthalmologist for evaluation.

5.3 Allergic Contact Dermatitis

Allergic contact dermatitis with corticosteroids is usually diagnosed by observing failure to heal rather than noting a clinical exacerbation. Such an observation should be corroborated with appropriate diagnostic patch testing.

5.4 Flammable Contents

Clobetasol propionate foam is flammable. Avoid fire, flame, or smoking during and immediately following application.

6 ADVERSE REACTIONS

The following adverse reactions are discussed in greater detail in other sections of the labeling:

- Effects on Endocrine System [see Warnings and Precautions (5.1)]
- Ophthalmic Adverse Reactions [see Warnings and Precautions (5.2)]

6.1 Clinical Trials Experience

Because clinical trials are conducted under widely varying conditions, adverse reaction rates observed in the clinical trials of a drug cannot be directly compared to rates in the clinical trials of another drug and may not reflect the rates observed in clinical practice.

In a controlled clinical trial involving 188 subjects with psoriasis of the scalp, there were no localized scalp adverse reactions reported in the subjects treated with clobetasol propionate foam. In 2 controlled clinical trials with clobetasol propionate foam in 360 subjects with psoriasis of non-scalp regions, localized adverse events that occurred in the subjects treated with clobetasol propionate foam included application site burning (10%), application site dryness (<1%), and other application site reactions (4%).

In larger controlled trials with other clobetasol propionate formulations, the most frequently reported local adverse reactions have included burning, stinging, irritation, pruritus, erythema, folliculitis, cracking and fissuring of the skin, numbness of the fingers, skin atrophy, and telangiectasia (all less than 2%).

6.2 Postmarketing Experience

Because adverse reactions are reported voluntarily from a population of uncertain size, it is not always possible to reliably estimate their frequency or establish a causal relationship to drug exposure.

Local adverse reactions to topical corticosteroids may include: striae, itching, acneiform eruptions, hypopigmentation, perioral dermatitis, allergic contact dermatitis, secondary infection, hypertrichosis, and miliaria.

Ophthalmic adverse reactions may include: cataracts, glaucoma, increased intraocular pressure, and central serous chorioretinopathy.

8 USE IN SPECIFIC POPULATIONS

8.1 Pregnancy

Risk Summary

There are no available data on clobetasol propionate foam use in pregnant women to inform of a drug-associated risk for adverse developmental outcomes.

Published data report a significantly increased risk of low birth weight with the use of greater than 300 grams of potent or very potent topical corticosteroid during a pregnancy. Advise pregnant women of the potential risk to a fetus and to use clobetasol propionate foam on the smallest area of skin and for the shortest duration possible (see Data). In animal reproduction studies, increased malformations, such as cleft palate and skeletal abnormalities, were observed after subcutaneous administration of clobetasol propionate to pregnant mice and rabbits. No comparison of animal exposure with human exposure was computed.

The estimated background risk of major birth defects and miscarriage for the indicated population is unknown. All pregnancies have a background risk of birth defect, loss, or other adverse outcomes. In the U.S. general population, the estimated background risk of major birth defects and miscarriage in clinically recognized pregnancies is 2 to 4% and 15 to 20%, respectively.

Data

Human Data

Multiple observational studies found no significant associations between maternal use of topical corticosteroids of any potency and congenital malformations, preterm delivery, or fetal mortality. However, when the dispensed amount of potent or very potent topical corticosteroid exceeded 300 g during the entire pregnancy, use was associated with an increase in low birth weight infants [adjusted RR, 7.74 (95% CI, 1.49 to 40.11)]. In addition, a small cohort study, in which 28 sub-Saharan women using potent topical corticosteroids (27/28 used clobetasol propionate 0.05%) for skin lightening during pregnancy, noted a higher incidence of low birth weight infants in the exposed group. The majority of exposed subjects treated large areas of the body (a mean quantity of 60 g/month (range, 12 to 170 g) over long periods of time.

Animal Data

Embryofetal development studies conducted with clobetasol propionate in mice using the subcutaneous route resulted in fetotoxicity at the highest dose tested (1 mg/kg) and malformations at all dose levels tested down to 0.03 mg/kg. Malformations seen included cleft palate and skeletal abnormalities.

In an embryofetal development study in rabbits, subcutaneous administration of clobetasol propionate resulted in malformations at doses of 0.003 and 0.01 mg/kg. Malformations seen included cleft palate, cranioschisis, and other skeletal abnormalities.

8.2 Lactation

Risk Summary

There is no information regarding the presence of clobetasol propionate in breast milk or its effects on the breastfed infant or on milk production. Systemically administered corticosteroids appear in human milk and can suppress growth, interfere with endogenous corticosteroid production, or cause other untoward effects. It is not known whether topical administration of clobetasol propionate could result in sufficient systemic absorption to produce detectable quantities in human milk. The developmental and health benefits of breastfeeding should be considered along with the mother’s clinical need for clobetasol propionate foam and any potential adverse effects on the breastfed infant from clobetasol propionate foam or from the underlying maternal condition.

Clinical Considerations

To minimize potential exposure to the breastfed infant via breast milk, use clobetasol propionate foam on the smallest area of skin and for the shortest duration possible while breastfeeding. Advise breastfeeding women not to apply clobetasol propionate foam directly to the nipple and areola to avoid direct infant exposure.

8.4 Pediatric Use

Safety and effectiveness of clobetasol propionate foam in patients younger than 12 years of age have not been established; therefore, use in children younger than 12 years is not recommended.

Because of a higher ratio of skin surface area to body mass, pediatric patients are at a greater risk than adults of systemic toxicity when they are treated with topical drugs. They are, therefore, also at greater risk of adrenal insufficiency upon the use of topical corticosteroids.

Rare systemic toxicities such as Cushing’s syndrome, linear growth retardation, delayed weight gain, and intracranial hypertension have been reported in pediatric patients especially those with prolonged exposure to large doses of high potency topical corticosteroids.

Local adverse reactions including striae have also been reported with use of topical corticosteroids in pediatric patients.

Avoid use of clobetasol propionate foam in the treatment of diaper dermatitis.

8.5 Geriatric Use

Clinical studies of clobetasol propionate foam did not include sufficient numbers of subjects aged 65 and over to determine whether they respond differently from younger subjects. Other reported clinical experience has not identified differences in responses between the elderly and younger patients. In general, dose selection for an elderly patient should be cautious, usually starting at the low end of the dosing range.

11 DESCRIPTION

Clobetasol Propionate Foam, 0.05%, is a white thermolabile hydroethanolic aerosol foam containing the active ingredient, clobetasol propionate, USP, a synthetic corticosteroid, for topical use. Clobetasol, an analog of prednisolone, has a high degree of glucocorticoid activity and a slight degree of mineralocorticoid activity.

Clobetasol propionate, USP is 21-chloro-9-fluoro-11ß,17-dihydroxy-16ß-methylpregna-1,4-diene-3,20-dione 17-propionate, with the molecular formula C25H32CIFO5, a molecular weight of 466.97 g/mol.

The following is the chemical structure:

Clobetasol propionate, USP is a white to almost white crystalline powder, practically insoluble in water, slightly soluble in benzene and diethyl ether; sparingly soluble in ethanol; freely soluble in acetone, in dimethylsulfoxide, in chloroform, in methanol and in dioxane.

Each gram of Clobetasol Propionate Foam, 0.05% contains 0.5 mg clobetasol propionate, USP. The foam also contains cetyl alcohol, citric acid, ethanol (60%), polysorbate 60, potassium citrate, propylene glycol, purified water, and stearyl alcohol pressurized with a hydrocarbon (propane/butane) propellant.

12 CLINICAL PHARMACOLOGY

12.1 Mechanism of Action

Corticosteroids play a role in cellular signaling, immune function, inflammation, and protein regulation; however, the precise mechanism of action in corticosteroid-responsive dermatoses is unknown.

12.2 Pharmacodynamics

In a controlled pharmacokinetic trial, 5 of 13 subjects experienced reversible suppression of the adrenals at any time during the 14 days of therapy with clobetasol propionate foam applied to at least 20% of involved body surface area. Of the 13 subjects studied, 1 of 9 with psoriasis was suppressed after 14 days and all 4 of the subjects with atopic dermatitis had abnormal cortisol levels indicative of adrenal suppression at some time after starting therapy with clobetasol propionate foam (See Table 1 below).

Table 1: Subjects With Reversible HPA Axis Suppression at Any Time During Treatment
Dermatosis | Clobetasol Propionate Foam
Psoriasis | 1 of 9
Atopic Dermatitisa | 4 of 4
a Clobetasol propionate foam is not indicated for non-scalp atopic dermatitis, as the safety and efficacy of clobetasol propionate foam in non-scalp atopic dermatitis has not been established. Use in children under 12 years of age is not recommended.

12.3 Pharmacokinetics

Topical corticosteroids can be absorbed from intact healthy skin. The extent of percutaneous absorption of topical corticosteroids is determined by many factors, including the product formulation and the integrity of the epidermal barrier. Occlusion, inflammation, and/or other disease processes in the skin may also increase percutaneous absorption. Once absorbed through the skin, topical corticosteroids are metabolized, primarily in the liver, and are then excreted by the kidneys. Some corticosteroids and their metabolites are also excreted in the bile.

13 NONCLINICAL TOXICOLOGY

13.1 Carcinogenesis, Mutagenesis, Impairment of Fertility

Long-term animal studies have not been performed to evaluate the carcinogenic potential of clobetasol propionate foam or clobetasol propionate.

In a 90-day repeat-dose toxicity study in rats, topical administration of clobetasol propionate foam at dose concentrations from 0.001% to 0.1% or from 0.03 to 0.3 mg/kg/day of clobetasol propionate resulted in a toxicity profile consistent with long-term exposure to corticosteroids including adrenal atrophy, histopathological changes in several organ systems indicative of severe immune suppression, and opportunistic fungal and bacterial infections. A no observable adverse effect level could not be determined in this study. Although the clinical relevance of the findings in animals to humans is not clear, sustained glucocorticoid-related immune suppression may increase the risk of infection and possibly the risk for carcinogenesis.

Clobetasol propionate was nonmutagenic in the Ames test, the mouse lymphoma test, the Saccharomyces cerevisiae gene conversion assay, and the E. coli B WP2 fluctuation test. In the in vivo mouse micronucleus test, a positive finding was observed at 24 hours, but not at 48 hours, following oral administration at a dose of 2,000 mg/kg.

Studies in the rat following subcutaneous administration of clobetasol propionate at dosage levels up to 0.05 mg/kg per day revealed that the females exhibited an increase in the number of resorbed embryos and a decrease in the number of living fetuses at the highest dose.

14 CLINICAL STUDIES

14.1 Scalp Psoriasis

A well-controlled clinical trial evaluated 188 subjects with moderate to severe scalp psoriasis. Subjects were treated twice daily for 2 weeks with one of 4 treatments: Clobetasol propionate foam, vehicle foam, a commercially available clobetasol propionate solution (TEMOVATE® Scalp Application), or vehicle solution. The efficacy of clobetasol propionate foam in treating scalp psoriasis at the end of the 2 weeks’ treatment was superior to that of vehicle (foam and solution), and was comparable to that of TEMOVATE Scalp Application (Table 2).

Table 2. Efficacy Results From a Controlled Clinical Trial in Scalp Psoriasis
 | Clobetasol Propionate Foam; n (%) | Vehicle Foam; n (%)
Total number of subjects | 62 | 31
Subjects with treatment successa | 39 (63) | 1 (3)
Subjects with parameter Clear at endpoint (scalp psoriasis)
Scaling - Clear at endpoint | 42 (68) | 3 (10)
Erythema - Clear at endpoint | 27 (44) | 2 (6)
Plaque Thickness - Clear at endpoint | 41 (66) | 3 (10)
a Defined as a composite of an Investigator's Global Assessment of "completely clear" or "almost clear," a plaque thickness score of 0, an erythema score of 0 or 1, and a scaling score of 0 or 1 at endpoint, scored on a severity scale of 0 to 4.

14.2 Non-scalp Psoriasis

Another well-controlled clinical trial evaluated 279 subjects with mild to moderate plaque-type psoriasis (mean body surface area at baseline was 6.7% with a range from 1% to 20%) of non-scalp regions. Subjects were treated twice daily for 2 weeks with clobetasol propionate foam or vehicle foam. The face and intertriginous areas were excluded from treatment. The efficacy of clobetasol propionate foam in treating non-scalp psoriasis at the end of 2 weeks’ treatment was superior to that of vehicle foam (Table 3).

Table 3. Efficacy Results From a Controlled Clinical Trial in Non-scalp Psoriasis
 | Clobetasol Propionate Foam; n (%) | Vehicle Foam; n (%)
Total number of subjects | 139 | 140
Subjects with treatment successa | 39 (28) | 4 (3)
Physician's Static Global Assessment -Clear or almost clear at endpoint | 94 (68) | 30 (21)
Scaling - Clear or almost clear at endpoint | 101 (73) | 42 (30)
Erythema - Clear or almost clear at endpoint | 88 (63) | 35 (25)
Plaque Thickness - Clear at endpoint | 44 (32) | 5 (4)
a Defined as a composite of a Physician’s Static Global Assessment score of 0 or 1, scaling score of 0 or 1, an erythema score of 0 or 1 and a plaque thickness score of 0, based on a severity scale of 0 to 5 at endpoint.

16 HOW SUPPLIED/STORAGE AND HANDLING

16.1 How Supplied

Clobetasol Propionate Foam, 0.05% contains 0.5 mg of clobetasol propionate, USP per gram. The white thermolabile hydroethanolic aerosol foam is available as follows:

- 50-g aluminum can - NDC 68462-608-27
- 100-g aluminum can - NDC 68462-608-94

16.2 Storage and Handling

Store at 20°C to 25°C (68°F to 77°F); excursions permitted to 15°C to 30°C (59°F to 86°F) [see USP Controlled Room Temperature].

FLAMMABLE. AVOID FIRE, FLAME, OR SMOKING DURING AND IMMEDIATELY FOLLOWING APPLICATION. Contents under pressure. Do not puncture or incinerate. Do not expose to heat or store at temperatures above 120°F (49°C).

Keep out of reach of children.

17 PATIENT COUNSELING INFORMATION

See FDA-approved patient labeling (Patient Information and Instructions for Use)

Effects on Endocrine System

Clobetasol propionate foam may cause HPA axis suppression. Advise patients that use of topical corticosteroids, including clobetasol propionate foam, may require periodic evaluation for HPA axis suppression. Topical corticosteroids may have other endocrine effects. Concomitant use of multiple corticosteroid-containing products may increase the total systemic exposure to topical corticosteroids. Patients should inform their physician(s) that they are using clobetasol propionate foam if surgery is contemplated [see Warnings and Precautions (5.1)].

Ophthalmic Adverse Reactions

Advise patients to report any visual symptoms to their healthcare providers [see Warnings and Precautions (5.2)].

Local Adverse Reactions

Report any signs of local adverse reactions to the physician. Advise patients that local reactions and skin atrophy are more likely to occur with occlusive use or prolonged use [see Warnings and Precautions (5.3)].

Pregnancy

Advise pregnant women of the potential risk to a fetus and to use clobetasol propionate foam on the smallest area of skin and for the shortest duration possible [see Use in Specific Populations (8.1)].

Lactation

Advise a woman to use clobetasol propionate foam on the smallest area of skin and for the shortest duration possible while breastfeeding. Advise breastfeeding women not to apply clobetasol propionate foam directly to the nipple and areola to avoid direct infant exposure [see Use in Specific Populations (8.2)].

Important Administration Instructions

Inform patients of the following:

- Avoid use of clobetasol propionate foam on the face, underarms, or groin areas unless directed by the physician.
- Do not occlude the treatment area with bandage or other covering, unless directed by the physician.
- Discontinue therapy when control is achieved. If no improvement is seen within 2 weeks, contact the physician.
- For proper dispensing of foam, hold the can upside down and depress the actuator. Dispensing directly onto hands is not recommended (unless the hands are the affected area), as the foam will begin to melt immediately upon contact with warm skin.
- Limit treatment to 2 consecutive weeks. Use no more than 50 grams of clobetasol propionate foam per week, or more than 21 capfuls per week.
- Avoid use of clobetasol propionate foam in the diaper area, as diapers or plastic pants may constitute occlusive dressing.
- The product is flammable; avoid heat, flame, and smoking when applying this product.
- Do not use other corticosteroid-containing products without first consulting with the physician.

For additional information, call Glenmark Pharmaceuticals Inc., USA at 1 (888) 721-7115.

*Trademarks are the property of their respective owners.

Distributed by:

Glenmark Pharmaceuticals Inc., USA

Elmwood Park, NJ 07407

Questions? 1 (888) 721-7115

www.glenmarkpharma-us.com

September 2025

Patient Information

Clobetasol Propionate

(kloe bay' ta sol proe' pee oh nate)

Foam

Important: Clobetasol propionate foam is for use on the skin only. Do not get clobetasol propionate foam in your eyes, mouth, or vagina.

What is clobetasol propionate foam?

Clobetasol propionate foam is a prescription corticosteroid medicine used in people 12 years of age and older for the treatment of:

- moderate to severe plaque psoriasis of the scalp and
- mild to moderate plaque psoriasis of the skin except the face and areas where the skin may touch or rub together.

It is not known if clobetasol propionate foam is safe and effective in children under 12 years of age. Clobetasol propionate foam is not recommended in children under 12 years of age.

Before using clobetasol propionate foam, tell your healthcare provider about all of your medical conditions, including if you:

- have had irritation or other skin reaction to a steroid medicine in the past.
- have a skin infection. You may need medicine to treat the skin infection before using clobetasol propionate foam.
- have diabetes.
- have adrenal gland problems.
- have liver problems.
- plan to have surgery.
- are pregnant or plan to become pregnant. It is not known if clobetasol propionate foam will harm your unborn baby. If you use clobetasol propionate foam during pregnancy, use clobetasol propionate foam on the smallest area of skin and for the shortest time needed.
- are breastfeeding or plan to breastfeed. It is not known if clobetasol propionate foam passes into your breast milk. If you use clobetasol propionate foam while breastfeeding, use clobetasol propionate foam on the smallest area of skin and for the shortest time needed. Do not apply clobetasol propionate foam directly to the nipple and areola to avoid getting clobetasol propionate foam into your baby’s mouth.

Tell your healthcare provider about all the medicine you take including prescription or over-the-counter medicines, vitamins, and herbal supplements. Do not use other products containing a corticosteroid medicine during treatment with clobetasol propionate foam without talking to your healthcare provider first.

How should I use clobetasol propionate foam?

See the “Instructions for Use” for detailed information about the right way to apply clobetasol propionate foam.

- Use clobetasol propionate foam exactly as your healthcare provider tells you to use it.
- Apply a thin layer of clobetasol propionate foam to the affected skin areas 2 times each day.
- Avoid using clobetasol propionate foam on your face, underarms (armpits), groin area, or in areas with thinning skin (atrophy).
- Avoid using clobetasol propionate foam on skin in a diaper area.
- Do not bandage or cover your treated area unless your healthcare provider tells you to.
- Do not use clobetasol propionate foam for longer than 2 weeks in a row.
- You should not use more than 50 grams or 21 capfuls of clobetasol propionate foam in 1 week.
- Talk to your healthcare provider if your skin or scalp does not improve after 2 weeks of treatment with clobetasol propionate foam.
- Wash your hands after using clobetasol propionate foam.

What should I avoid while using clobetasol propionate foam?

Clobetasol propionate foam is flammable. Avoid heat, flame, or smoking during and right after you apply clobetasol propionate foam to your skin.

What are the possible side effects of clobetasol propionate foam?

Clobetasol propionate foam may cause serious side effects, including:

- Clobetasol propionate foam can pass through your skin. Too much clobetasol propionate foam passing through your skin can cause adrenal glands to stop working.
- Cushing’s syndrome, a condition that happens when the body is exposed to too much of the hormone cortisol.
- High blood sugar (hyperglycemia)
- Vision problems. Clobetasol propionate foam may increase your chance of developing vision problems such as cataract(s) and glaucoma. Tell your healthcare provider if you develop blurred vision or other vision problems during treatment with clobetasol propionate foam.
- Skin reactions at the treated skin site. Tell your healthcare provider if you get any skin reactions or skin infections.
- Effects on growth and weight in children.

Your healthcare provider may do certain blood tests to check for side effects.

The most common side effects of clobetasol propionate foam include burning and skin reactions at the treated site. These are not all the possible side effects of clobetasol propionate foam.

Call your healthcare provider for medical advice about side effects. You may report side effects to FDA at 1-800-FDA-1088.

How should I store clobetasol propionate foam?

- Store clobetasol propionate foam at room temperature between 68°F to 77°F (20°C to 25°C).
- Do not break through (puncture) the clobetasol propionate foam can.
- Never throw the can into a fire, even if the can is empty.
- Do not store clobetasol propionate foam near heat or store at temperatures above 120°F (49°C).

Keep clobetasol propionate foam and all medicines out of the reach of children.

General information about the safe and effective use of clobetasol propionate foam.

Medicines are sometimes prescribed for purposes other than those listed in a Patient Information leaflet. Do not use clobetasol propionate foam for a condition for which it was not prescribed. Do not give clobetasol propionate foam to other people, even if they have the same condition that you have. It may harm them. You can ask your healthcare provider or pharmacist for information about clobetasol propionate foam that is written for health professionals.

What are the ingredients in clobetasol propionate foam?

Active ingredient: clobetasol propionate

Inactive ingredients: cetyl alcohol, citric acid, ethanol (60%), polysorbate 60, potassium citrate, propylene glycol, purified water, and stearyl alcohol pressurized with a hydrocarbon (propane/butane) propellant.

Distributed by:

Glenmark Pharmaceuticals Inc., USA

Elmwood Park, NJ 07407

Questions? 1 (888) 721-7115

www.glenmarkpharma-us.com

September 2025

Instructions for Use

Clobetasol Propionate

(kloe bay' ta sol proe' pee oh nate)

Foam

Important: Clobetasol propionate foam is for use on the skin only. Do not get clobetasol propionate foam in your eyes, mouth or vagina.

How to apply clobetasol propionate foam:

Figure A

Step 1: Remove the cap and save for further use.

Step 2: Before applying clobetasol propionate foam for the first time, break the tiny plastic piece at the base of the can’s rim by gently pushing back (away from the piece) on the nozzle. (see Figure A)

Figure B

Step 3: Turn the can upside down. Push the button to dispense a small amount of clobetasol propionate foam into the cap of the can, or on your affected skin area. (see Figure B) This amount should be no more than 1½ capfuls, about the size of a golf ball.

- Do not dispense clobetasol propionate foam directly onto your hands (unless your hands are the affected areas), because the foam will begin to melt right away on contact with your warm skin.
- If your fingers are warm, rinse them in cold water first. Be sure to dry them thoroughly before handling the foam.
- If the can seems warm or the foam seems runny, run the can under cold water.
- Do not dispense clobetasol propionate foam in horizontal and upright orientation.

Figure C

Step 4: Using your fingertips, gently massage a thin layer of clobetasol propionate foam into the affected skin areas until the foam disappears. (see Figures C and D)

Figure D

Figure E

Step 5: If you are treating areas with hair, such as the scalp, move any hair away so that the foam can be applied directly to the affected areas. (see Figure E)

- Repeat until the affected areas are treated.

Keep the foam away from your eyes, as it will sting and may cause eye problems if there is frequent contact with your eyes. If the foam gets in your eyes, rinse them well with cold water right away. If the stinging continues, contact your healthcare provider right away.

Figure F

Step 6: Wash your hands after applying clobetasol propionate foam. (see Figure F)

- Throw away any of the unused medicine that you dispensed out of the can.

This Instructions for Use has been approved by the U.S. Food and Drug Administration.

Distributed by:

Glenmark Pharmaceuticals Inc., USA

Elmwood Park, NJ 07407

Questions? 1 (888) 721-7115

www.glenmarkpharma-us.com

September 2025